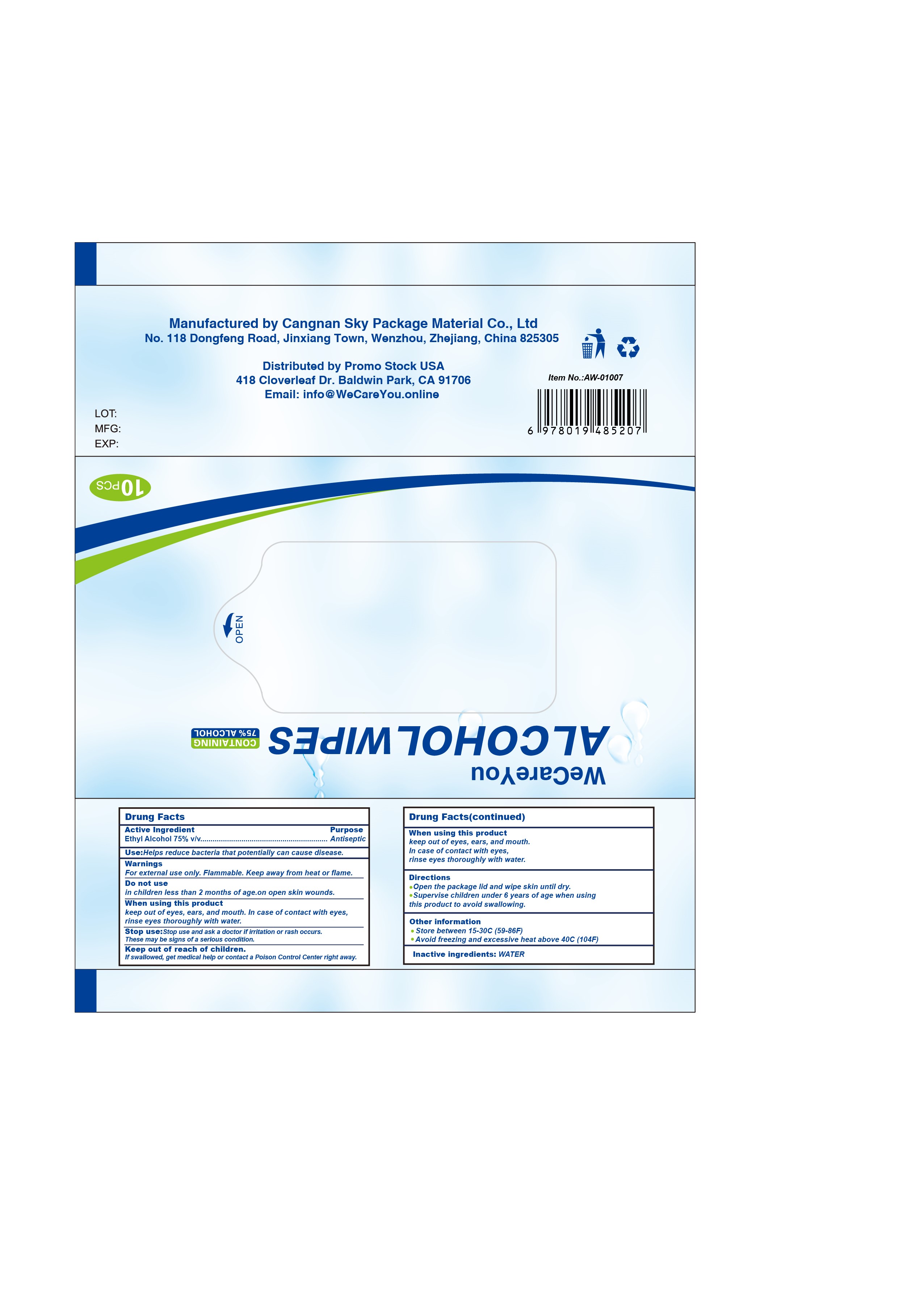 DRUG LABEL: WeCareYou Alcohol Wipes
NDC: 78019-520 | Form: CLOTH
Manufacturer: Cangnan Sky Package Material Co., Ltd
Category: otc | Type: HUMAN OTC DRUG LABEL
Date: 20200603

ACTIVE INGREDIENTS: ALCOHOL 75 mL/100 mL
INACTIVE INGREDIENTS: WATER

Cangnan Sky Package Material Co., Ltd

Active Ingredient

Ethyl Alcohol 75% v/v

Purpose

Ethyl Alcohol Antiseptic

Use

Helps reduce bacteria that potentially can cause disease.

Warnings

For external use only. Flammable. Keep away from heat or flame.

Do not use

- in children less than 2 months of age.
- on open skin wounds.

When using this product

keep out of eyes, ears, and mouth. In case of contact with eyes, rinse eyes thoroughly with water.

Stop use

Stop use and ask a doctor if irritation or rash occurs. These may be signs of a serious condition.

Keep out of reach of children.

If swallowed, get medical help or contact a Poison Control Center right away.

Directions

- Open the package lid and wipe skin until dry.
- Supervise children under 6 years of age when using this product to avoid swallowing.

Other information

- Store between 15-30C (59-86F)
- Avoid freezing and excessive heat above 40C (104F)

Manufactured by Cangnan Sky Package Material Co., Ltd
No. 118 Dongfeng Road, Jinxiang Town, Wenzhou, Zhejiang, China 825305

Distributed by Promo Stock USA
418 Cloverleaf Dr. Baldwin Park, CA 91706
Phone: (626)330-1688
Email: shellyli@promostockusa.com

Inactive ingredients

WATER